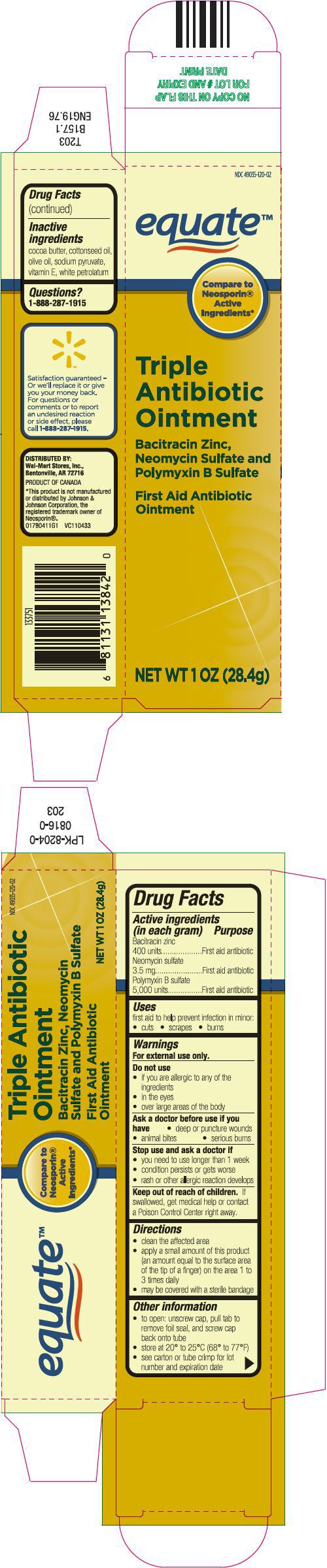 DRUG LABEL: Triple Antibiotic
NDC: 49035-120 | Form: OINTMENT
Manufacturer: Wal-Mart Stores, Inc.
Category: otc | Type: HUMAN OTC DRUG LABEL
Date: 20170713

ACTIVE INGREDIENTS: Bacitracin Zinc 400 [iU]/1 g; Neomycin Sulfate 3.5 mg/1 g; Polymyxin B Sulfate 5000 [iU]/1 g
INACTIVE INGREDIENTS: cocoa butter; cottonseed oil; olive oil; sodium pyruvate; .ALPHA.-TOCOPHEROL; petrolatum

Triple Antibiotic

Drug Facts

ACTIVE INGREDIENT

Active ingredients (in each gram) | Purpose
Bacitracin zinc 400 units | First aid antibiotic
Neomycin sulfate 3.5 mg | First aid antibiotic
Polymyxin B sulfate 5,000 units | First aid antibiotic

Uses

first aid to help prevent infection in minor:

- cuts
- scrapes
- burns

Warnings

For external use only.

Do not use

- if you are allergic to any of the ingredients
- in the eyes
- over large areas of the body

Ask a doctor before use if you have

- deep or puncture wounds
- animal bites
- serious burns

Stop use and ask a doctor if

- you need to use longer than 1 week
- condition persists or gets worse
- rash or other allergic reaction develops

Keep out of reach of children. If swallowed, get medical help or contact a Poison Control Center right away.

Directions

- clean the affected area
- apply a small amount of this product (an amount equal to the surface area of the tip of a finger) on the area 1 to 3 times daily
- may be covered with a sterile bandage

Other information

- to open: unscrew cap, pull tab to remove foil seal, and screw cap back onto tube
- store at 20° to 25°C (68° to 77°F)
- see carton or tube crimp for lot number and expiration date

Inactive ingredients

cocoa butter, cottonseed oil, olive oil, sodium pyruvate, vitamin E, white petrolatum

Questions?

1-888-287-1915

DISTRIBUTED BY:
Wal-Mart Stores, Inc.,
Bentonville, AR 72716

PRINCIPAL DISPLAY PANEL - 28.4 g Tube Carton

NDC 49035-120-02

equate™

Compare to
Neosporin®
Active
Ingredients*

Triple
Antibiotic
Ointment

Bacitracin Zinc,
Neomycin Sulfate and
Polymyxin B Sulfate

First Aid Antibiotic
Ointment

NET WT 1 OZ (28.4g)